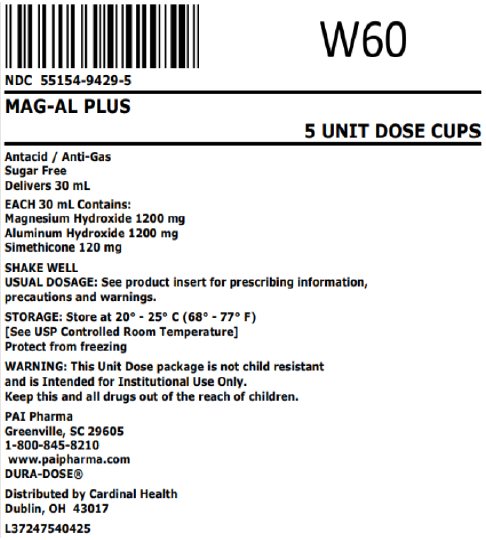 DRUG LABEL: Mag-Al Plus
NDC: 55154-9429 | Form: SUSPENSION
Manufacturer: Cardinal Health 107, LLC
Category: otc | Type: HUMAN OTC DRUG LABEL
Date: 20250501

ACTIVE INGREDIENTS: ALUMINUM HYDROXIDE 200 mg/5 mL; MAGNESIUM HYDROXIDE 200 mg/5 mL; DIMETHICONE, UNSPECIFIED 20 mg/5 mL
INACTIVE INGREDIENTS: BUTYLPARABEN; HYPROMELLOSE, UNSPECIFIED; PROPYLENE GLYCOL; PROPYLPARABEN; WATER; SACCHARIN SODIUM; SORBITOL

Mag-AL Plus

Drug Facts

ACTIVE INGREDIENT

PURPOSE

Active ingredients (in each 5 mL = 1 teaspoonful) | Purpose
Aluminum hydroxide (equiv. to dried gel, USP) 200 mg | Antacid
Magnesium hydroxide 200 mg | Antacid
Simethicone 20 mg | Antigas

Uses

for the relief of:

- acid indigestion
- heartburn
- sour stomach
- upset stomach due to these symptoms
- pressure and bloating commonly referred to as gas

Warnings

Do not take more than 16 teaspoonfuls in a 24-hour period or use the maximum dosage for more than 2 weeks except under the advice and supervision of a physician.

Ask a doctor before use if you have

- kidney disease
- a magnesium-restricted diet

Ask a doctor or pharmacist before use if you are presently taking a prescription drug. Antacids may interact with certain prescription drugs.

Stop use and ask a doctor if symptoms last more than 2 weeks.

Keep out of reach of children.

Directions

- shake well before using
- do not take more than 16 teaspoonfuls in 24 hours or use the maximum dosage for more than 2 weeks

adults and children 12 years and older | take 2 to 4 teaspoonfuls four times a day or as directed by a physician
children under 12 years | consult a physician

Other information

- each 5 mL contains: magnesium 83 mg, sodium 1.34 mg
- store at controlled room temperature 20° - 25°C (68° - 77°F)
- protect from freezing
- White colored, peppermint flavored liquid supplied in the following oral dosage form:
  Overbagged with 5 x 30 mL unit dose cups in each bag, NDC 55154-9429-5
  WARNING: This Unit Dose package is not child resistant and is Intended for Institutional Use Only. Keep this and all drugs out of the reach of children.

Inactive ingredients

Butylparaben, hydroxypropyl methylcellulose, flavoring, propylene glycol, propylparaben, purified water, sodium saccharin, and sorbitol solution.

Questions or comments?

Call 1-800-845-8210

MANUFACTURED BY

Pharmaceutical
Associates, Inc.
Greenville, SC 29605

Distributed By:

Cardinal Health

Dublin, OH 43017

L37247540425

Principal Display Panel

NDC 55154-9429-5

MAG-AL PLUS

5 UNIT DOSE CUPS